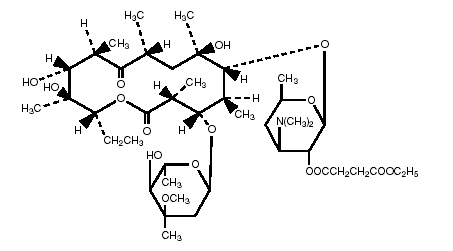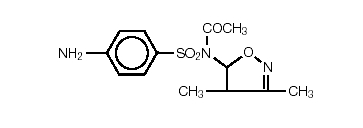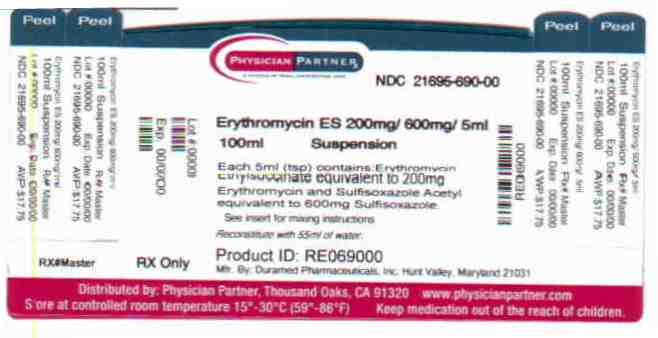 DRUG LABEL: ERYTHROMYCIN ETHYLSUCCINATE AND SULFISOXAZOLE ACETYL
NDC: 21695-690 | Form: GRANULE, FOR SUSPENSION
Manufacturer: Rebel Distributors Corp
Category: prescription | Type: HUMAN PRESCRIPTION DRUG LABEL
Date: 20110117

ACTIVE INGREDIENTS: ERYTHROMYCIN ETHYLSUCCINATE 200 mg/5 mL; SULFISOXAZOLE ACETYL 600 mg/5 mL
INACTIVE INGREDIENTS: LACTOSE, ANHYDROUS; METHYLPARABEN; POLYSORBATE 80; POVIDONE; ANHYDROUS TRISODIUM CITRATE; SUCROSE

ERYTHROMYCIN ETHYLSUCCINATE AND SULFISOXAZOLE ACETYL FOR ORAL SUSPENSION, USP

Revised MARCH 2007
11001190

Rx only

DESCRIPTION:

Erythromycin ethylsuccinate and sulfisoxazole acetyl, when reconstituted with water as directed on the label, the granules form a white, cherry flavored suspension that provides the equivalent of 200 mg erythromycin activity and the equivalent of 600 mg of sulfisoxazole activity per teaspoonful (5 mL).

Erythromycin is produced by a strain of Saccaropolyspora erythraea and belongs to the macrolide group of antibiotics. It is basic and readily forms salts and esters. Erythromycin ethylsuccinate is the 2’-ethylsuccinyl ester of erythromycin. It is essentially a tasteless form of the antibiotic suitable for oral administration, particularly in suspension dosage forms. The chemical name is erythromycin 2’-(ethylsuccinate). Erythromycin ethylsuccinate has the following structural formula:

C45H75NO16 Molecular Weight: 862.06

Sulfisoxazole acetyl or N^1-acetyl sulfisoxazole is an ester of sulfisoxazole. Chemically, sulfisoxazole is N^1-(3,4-dimethyl-5-isoxazotyl) sulfanilamide. Sulfisoxazole acetyl has the following structural formula:

C13H15N3O4S Molecular Weight: 309.34

Inactive Ingredients:

Artificial flavor, lactose anhydrous, methylparaben, polysorbate 80, povidone, simethicone, sodium citrate anhydrous and sucrose.

CLINICAL PHARMACOLOGY:

Orally administered erythromycin ethylsuccinate suspensions are readily and reliably absorbed. Erythromycin ethylsuccinate products have demonstrated rapid and consistent absorption in both fasting and nonfasting conditions. However, higher serum concentrations are obtained when these products are given with food. Erythromycin is largely bound to plasma proteins. After absorption, erythromycin diffuses readily into most body fluids. In the absence of meningeal inflammation, low concentrations are normally achieved in the spinal fluid, but the passage of the drug across the blood-brain barrier increases in meningitis. Erythromycin crosses the placental barrier and is excreted in human milk. Erythromycin is not removed by peritoneal dialysis or hemodialysis.

In the presence of normal hepatic function, erythromycin is concentrated in the liver and is excreted in the bile; the effect of hepatic dysfunction on biliary excretion of erythromycin is not known. After oral administration, less than 5% of the administered dose can be recovered in the active form in the urine.

Wide variation in blood levels may result following identical doses of a sulfonamide. Blood levels should be measured in patients receiving these drugs for serious infections. Free sulfonamide blood levels of 50 to 150 mcg/mL may be considered therapeutically effective for most infections, with blood levels of 120 to 150 mcg/mL being optimal for serious infections. The maximum sulfonamide level should be 200 mcg/mL, because adverse reactions occur more frequently above this concentration.

Following oral administration, sulfisoxazole is rapidly and completely absorbed; the small intestine is the major site of absorption, but some of the drug is absorbed from the stomach. Sulfonamides are present in the blood as free, conjugated (acetylated and possibly other forms), and protein-bound forms. The amount present as “free” drug is considered to be the therapeutically active form. Approximately 85% of a dose of sulfisoxazole is bound to plasma proteins, primarily to albumin; 65% to 72% of the unbound portion is in the nonacetylated form.

Maximum plasma concentrations of intact sulfisoxazole following a single 2 g oral dose of sulfisoxazole to healthy adult volunteers ranged from 127 to 211 mcg/mL (mean 169 mcg/mL), and the time of peak plasma concentration ranged from 1 to 4 hours (mean, 2.5 hours). The elimination half-life of sulfisoxazole ranged from 4.6 to 7.8 hours after oral administration. The elimination of sulfisoxazole has been shown to be slower in elderly subjects (63 to 75 years) with diminished renal function (creatine clearance 37 to 68 mL/min).^1 After multiple-dose oral administration of 500 mg q.i.d. to healthy volunteers, the average steady-state plasma concentrations of intact sulfisoxazole ranged from 49.9 to 88.8 mcg/mL (mean 63.4 mcg/mL).^2

Sulfisoxazole and its acetylated metabolites are excreted primarily by the kidneys through glomerular filtration. Concentrations of sulfisoxazole are considerably higher in the urine than in the blood. The mean urinary recovery following oral administration of sulfisoxazole is 97% within 48 hours; 52% of this is intact drug, and the remainder is the N^4-acetylated metabolite.

Sulfisoxazole is distributed only in extracellular body fluids. It is excreted in human milk. It readily crosses the placental barrier. In healthy subjects, cerebrospinal fluid concentrations of sulfisoxazole vary; in patients with meningitis, however, concentrations of free drug in cerebrospinal fluid as high as 94 mcg/mL have been reported.

Microbiology:

This product has been formulated to contain sulfisoxazole for concomitant use with erythromycin.

Erythromycin acts by inhibition of protein synthesis by binding 50 S ribosomal sub-units of susceptible organisms. It does not affect nucleic acid synthesis. Antagonism has been demonstrated in vitro between erythromycin and clindamycin, lincomycin, and chloramphenicol.

The sulfonamides are bacteriostatic agents, and the spectrum of activity is similar for all. Sulfonamides inhibit bacterial synthesis of dihydrofolic acid by preventing the condensation of the pteridine with para-aminobenzoic acid through competitive inhibition of the enzyme dihydropteroate synthetase. Resistant strains have altered dihydropteroate synthetase with reduced affinity for sulfonamides or produce increased quantities of para-aminobenzoic acid.

Susceptibility Testing:

Quantitative methods that require measurement of zone diameter give the most precise estimates of the susceptibility of bacteria to antimicrobial agents. One such standardized single-disc procedure^3 has been recommended for use with discs to test susceptibility to erythromycin and sulfisoxazole. Interpretation involves correlation of the zone diameters obtained in the disc test with minimal inhibitory concentration (MIC) values for erythromycin and sulfisoxazole.

If the standardized procedure of disc susceptibility is used, a 15 mcg erythromycin disc should give a zone diameter of at least 18 mm when tested against an erythromycin-susceptible bacterial strain, and a 250-300 mcg sulfisoxazole disc should give a zone diameter of at least 17 mm when tested against a sulfisoxazole-susceptible bacterial strain.

In vitro sulfonamides susceptibility tests are not always reliable because media containing excessive amounts of thymidine are capable of reversing the inhibitory effect of sulfonamides, which may result in false resistant reports. The tests must be carefully coordinated with bacteriological and clinical responses. When the patient is already taking sulfonamides, follow-up cultures should have aminobenzoic acid added to the isolation media but not to subsequent susceptibility test media.

INDICATIONS AND USAGE:

For treatment of ACUTE OTITIS MEDIA in children that is caused by susceptible strains of Haemophilus influenzae.

CONTRAINDICATIONS:

Erythromycin ethylsuccinate and sulfisoxazole acetyl for oral suspension is contraindicated in the following patient populations:

Patients with a known hypersensitivity to either of its components, children younger than 2 months, pregnant women at term, and mothers nursing infants less than 2 months of age.

Use in pregnant women at term, in children less than 2 months of age, and in mothers nursing infants less than 2 months of age is contraindicated because sulfonamides may promote kernicterus in the newborn by displacing bilirubin from plasma proteins.

Erythromycin is contraindicated in patients taking terfenadine. (See PRECAUTIONS, Drug Interactions:.)

WARNINGS:

FATALITIES ASSOCIATED WITH THE ADMINISTRATION OF SULFONAMIDES, ALTHOUGH RARE, HAVE OCCURRED DUE TO SEVERE REACTIONS, INCLUDING STEVENS-JOHNSON SYNDROME, TOXIC EPIDERMAL NECROLYSIS, FULMINANT HEPATIC NECROSIS, AGRANULOCYTOSIS, APLASTIC ANEMIA, AND OTHER BLOOD DYSCRASIAS.

SULFONAMIDES, INCLUDING SULFONAMIDE-CONTAINING PRODUCTS SUCH AS ERYTHROMYCIN ETHYLSUCCINATE AND SULFISOXAZOLE ACETYL FOR ORAL SUSPENSION, SHOULD BE DISCONTINUED AT THE FIRST APPEARANCE OF SKIN RASH OR ANY SIGN OF ADVERSE REACTION. In rare instances, a skin rash may be followed by a more severe reaction, such as Stevens-Johnson syndrome, toxic epidermal necrolysis, hepatic necrosis, and serious blood disorders. (See PRECAUTIONS.)

Clinical signs such as sore throat, fever, pallor, rash, purpura, or jaundice may be early indications of serious reactions.

There have been reports of hepatic dysfunction, with or without jaundice, occurring in patients receiving oral erythromycin products.

Cough, shortness of breath, and pulmonary infiltrates are hypersensitivity reactions of the respiratory tract that have been reported in association with sulfonamide treatment.

The sulfonamides should not be used for the treatment of group A beta-hemolytic streptococcal infections. In an established infection, they will not eradicate the streptococcus and, therefore, will not prevent sequelae such as rheumatic fever.

Pseudomembranous colitis has been reported with nearly all antibacterial agents, including erythromycin ethylsuccinate and sulfisoxazole acetyl for oral suspension, and may range in severity from mild to life-threatening. Therefore, it is important to consider this diagnosis in patients who present with diarrhea subsequent to the administration of antibacterial agents.

Treatment with antibacterial agents alters the normal flora of the colon and may permit overgrowth of clostridia. Studies indicate that a toxin produced by Clostridium difficile is one primary cause of “antibiotic-associated colitis”.

After diagnosis of pseudomembranous colitis has been established, therapeutic measures should be initiated. Mild cases of pseudomembranous colitis usually respond to drug discontinuation alone. In moderate to severe cases, consideration should be given to management with fluids and electrolytes, protein supplementation, and treatment with an antibacterial drug clinically effective against Clostridium difficile colitis.

There have been reports suggesting that erythromycin does not reach the fetus in adequate concentration to prevent congenital syphilis. Infants born to women treated during pregnancy with erythromycin for early syphilis should be treated with an appropriate penicillin regimen.

Rhabdomyolysis with or without renal impairment has been reported in seriously ill patients receiving erythromycin concomitantly with lovastatin. Therefore, patients receiving concomitant lovastatin and erythromycin should be carefully monitored for creatine kinase (CK) and serum transaminase levels. (See package insert for lovastatin.)

PRECAUTIONS:

General:

Erythromycin is principally excreted by the liver. Caution should be exercised when erythromycin is administered to patients with impaired hepatic function. (See CLINICAL PHARMACOLOGY and WARNINGS sections.)

Prolonged or repeated use of erythromycin may result in an overgrowth of nonsusceptible bacteria or fungi. If superinfection occurs, erythromycin should be discontinued and appropriate therapy instituted.

There have been reports that erythromycin may aggravate the weakness of patients with myasthenia gravis.

When indicated, incision and drainage or other surgical procedures should be performed in conjunction with antibiotic therapy.

Sulfonamides should be given with caution to patients with impaired renal or hepatic function and to those with severe allergy or bronchial asthma. In glucose-6-phosphate dehydrogenase-deficient individuals, hemolysis may occur; this reaction is frequently dose-related.

Information For Patients:

Patients should maintain an adequate fluid intake to prevent crystalluria and stone formation.

Laboratory Tests:

Complete blood counts should be done frequently in patients receiving sulfonamides. If a significant reduction in the count of any formed blood element is noted, erythromycin ethylsuccinate and sulfisoxazole acetyl for oral suspension should be discontinued. Urinalysis with careful microscopic examination and renal function tests should be performed during therapy, particularly for those patients with impaired renal function. Blood levels should be measured in patients receiving a sulfonamide for serious infections. (See INDICATIONS AND USAGE.)

Drug Laboratory Test Interactions:

Erythromycin interferes with the fluorometric determination of urinary catecholamines.

Drug Interactions:

Erythromycin use in patients who are receiving high doses of theophylline may be associated with an increase in serum theophylline levels and potential theophylline toxicity. In case of theophylline toxicity and/or elevated serum theophylline levels, the dose of theophylline should be reduced while the patient is receiving concomitant erythromycin therapy.

Concomitant administration of erythromycin and digoxin has been reported to result in elevated digoxin serum levels.

There have been reports of increased anticoagulant effects when erythromycin and oral anticoagulants were used concomitantly. Increased anticoagulation effects due to this drug may be more pronounced in the elderly.

Concurrent use of erythromycin and ergotamine or dihydroergotamine has been associated in some patients with acute ergot toxicity characterized by severe peripheral vasospasm and dysesthesia.

Erythromycin has been reported to decrease the clearance of triazolam and midazolam and thus may increase the pharmacologic effect of these benzodiazepines.

The use of erythromycin in patients concurrently taking drugs metabolized by the cytochrome P450 system may be associated with elevations in serum levels of these other drugs. There have been reports of interactions of erythromycin with carbamazepine, cyclosporine, hexobarbital, phenytoin, allentanil, diisopyramide, lovastatin, and bromocriptine. Serum concentrations of drugs metabolized by the cytochrome P450 system should be monitored closely in patients concurrently receiving erythromycin.

Erythromycin significantly alters the metabolism of terfenadine when taken concomitantly. Rare cases of serious cardiovascular adverse events, including death, cardiac arrest, torsades de pointes, and other ventricular arrhythmias, have been observed. (See CONTRAINDICATIONS.)

It has been reported that sulfisoxazole may prolong the prothrombin time in patients who are receiving the anticoagulant warfarin. This interaction should be kept in mind when erythromycin ethylsuccinate and sulfisoxazole acetyl for oral suspension is given to patients already on anticoagulant therapy, and the coagulation time should be reassessed.

It has been proposed that sulfisoxazole competes with thiopental for plasma protein binding. In one study involving 48 patients, intravenous sulfisoxazole resulted in a decrease in the amount of thiopental required for anesthesia and in a shortening of the awakening time. It is not known whether chronic oral doses of sulfisoxazole have a similar effect. Until more is known about this interaction, physicians should be aware that patients receiving sulfisoxazole might require less thiopental for anesthesia.

Sulfonamides can displace methotrexate from plasma protein binding sites, thus increasing free methotrexate concentrations. Studies in man have shown sulfisoxazole infusions to decrease plasma protein-bound methotrexate by one fourth.

Sulfisoxazole can also potentiate the blood-sugar-lowering activity of sulfonylureas.

Carcinogenesis, Mutagenesis, Impairment of Fertility:

Carcinogenesis:

Erythromycin ethylsuccinate and sulfisoxazole acetyl for oral suspension has not undergone adequate trials relating to carcinogenicity: each component, however, has been evaluated separately. Long-term (21 month) oral studies conducted in rats with erythromycin ethylsuccinate did not provide evidence of tumorigenicity. Sulfisoxazole was not carcinogenic in either sex when administered to mice by gavage for 103 weeks at dosages up to approximately 18 times the recommended human dose or to rats at 4 times the human dose. Rats appear to be especially susceptible to the goitrogenic effects of sulfonamides, and long-term administration of sulfonamides has resulted in thyroid malignancies in this species.

Mutagenesis:

There are no studies available that adequately evaluate the mutagenic potential of erythromycin ethylsuccinate and sulfisoxazole acetyl for oral suspension or either of its components. However, sulfisoxazole was not observed to be mutagenic in E. coli Sd-4-73 when tested in the absence of a metabolic activating system. There was no apparent effect on male or female fertility in rats fed erythromycin (base) at levels up to 0.25% of diet.

Impairment of Fertility:

Erythromycin ethylsuccinate and sulfisoxazole acetyl for oral suspension has not undergone adequate trials relating to impairment of fertility. In a reproduction study in rats given 7 times the human dose per day of sulfisoxazole, no effects were observed regarding mating behavior, conception rate or fertility index (percent pregnant).

Pregnancy:

Teratogenic Effects:

Pregnancy Category C:

At dosages 7 times the human daily dose, sulfisoxazole was not teratogenic in either rats or rabbits. However, in two other teratogenicity studies, cleft palates developed in both rats and mice after administration of 5 to 9 times the human therapeutic dose of sulfisoxazole.

There is no evidence of teratogenicity or any other adverse effects on reproduction in female rats fed erythromycin base (up to 0.25% of diet) prior to and during mating, during gestation, and through weaning of two successive litters. There are, however, no adequate and well-controlled studies in pregnant women. Because animal reproduction studies are not always predictive of human response, this drug should be used during pregnancy only if clearly needed. Erythromycin has been reported to cross the placental barrier in humans, but fetal plasma levels are generally low.

There are no adequate or well-controlled studies of erythromycin ethylsuccinate and sulfisoxazole acetyl for oral suspension in either laboratory animals or in pregnant women. It is not known whether erythromycin ethylsuccinate and sulfisoxazole acetyl for oral suspension can cause fetal harm when administered to a pregnant woman prior to term or can affect reproduction capacity. Erythromycin ethylsuccinate and sulfisoxazole acetyl for oral suspension should be used during pregnancy only if the potential benefit justifies the potential risk to the fetus.

Nonteratogenic Effects:

Kernicterus may occur in the newborn as a result of treatment of a pregnant woman at term with sulfonamides. (See CONTRAINDICATIONS:.)

Labor and Delivery:

The effects of erythromycin and sulfisoxazole on labor and delivery are unknown.

Nursing Mothers:

Both erythromycin and sulfisoxazole are excreted in human milk. Because of the potential for the development of kernicterus in neonates due to the displacement of bilirubin from plasma proteins by sulfisoxazole, a decision should be made whether to discontinue nursing or discontinue the drug, taking into account the importance of the drug to the mother. (See CONTRAINDICATIONS:

Pediatric Use:

See INDICATIONS AND USAGE and DOSAGE AND ADMINISTRATION sections. Not for use in children under 2 months of age. (See CONTRAINDICATIONS.)

ADVERSE REACTIONS:

Erythromycin Ethylsuccinate:

The most frequent side effects of oral erythromycin preparations are gastrointestinal and are dose-related. They include nausea, vomiting, abdominal pain, diarrhea and anorexia. Symptoms of hepatic dysfunction and/or abnormal liver-function test results may occur (see WARNINGS section). Pseudomembranous colitis has been rarely reported in association with erythromycin therapy.

Allergic reactions ranging from urticaria and mild skin eruptions to anaphylaxis have occurred.

There have been isolated reports of reversible hearing loss occurring chiefly in patients with renal insufficiency and in patients receiving high doses of erythromycin.

Onset of pseudomembranous colitis symptoms may occur during of after antibiotic treatment. (See WARNINGS.)

Sulfisoxazole Acetyl:

Included in the listing that follows are adverse reactions that have been reported with other sulfonamide products: pharmacologic similarities require that each of the reactions be considered with erythromycin ethylsuccinate and sulfisoxazole acetyl for oral suspension administration.

Allergic/Dermatologic:

Anaphylaxis, erythema multiforme (Stevens-Johnson syndrome), toxic epidermal necrolysis (Lyell’s syndrome), exfoliative dermatitis, angioedema, arteritis, vasculitis, allergic myocarditis, serum sickness, rash, urticaria, pruritus, photosensitivity, and conjunctival and scleral injection. In addition, periarteritis nodosa and systemic lupus erythematosus have been reported. (See WARNINGS.)

Cardiovascular:

Tachycardia, palpitations, syncope, and cyanosis.

Rarely, erythromycin has been associated with the production of ventricular arrhythmias, including ventricular tachycardia and torsade de pointes, in individuals with prolonged QT intervals.

Endocrine:

The sulfonamides bear certain chemical similarities to some goitrogens, diuretics (acetazolamide and the thiazides) and oral hypoglycemic agents. Cross-sensitivity may exist with these agents. Developments of goiter, diuresis, and hypoglycemia has occurred rarely in patients receiving sulfonamides.

Gastrointestinal:

Hepatitis, hepatocellular necrosis, jaundice, pseudomembranous colitis, nausea, emesis, anorexia, abdominal pain, diarrhea, gastrointestinal hemorrhage, melena, flatulence, glossitis, stomatitis, salivary gland enlargement, and pancreatitis. Onset of pseudomembranous colitis symptoms may occur during or after treatment with sulfisoxazole, a component of erythromycin ethylsuccinate and sulfisoxazole acetyl for oral suspension. (See WARNINGS.)

The sulfisoxazole acetyl component of erythromycin ethylsuccinate and sulfisoxazole acetyl for oral suspension has been reported to cause increased elevation of liver-associated enzymes in patients with hepatitis.

Genitourinary:

Crystalluria, hematuria, BUN and creatinine elevations, nephritis, and toxic nephrosis with oliguria and anuria. Acute renal failure and urinary retention have also been reported.

The frequency of renal complications, commonly associated with some sulfonamides, is lower in some patients receiving the more soluble sulfonamides such as sulfisoxazole.

Hematologic:

Leukopenia, agranulocytosis, aplastic anemia, thrombocytopenia, purpura, hemolytic anemia, anemia, eosinophilia, clotting disorders including hypopro-thrombinemia and hypofibrinogenemia, sulfhemoglobinemia, and methemoglobinemia.

Neurologic:

Headache, dizziness, peripheral neuritis, paresthesia, convulsions, tinnitus, vertigo, ataxia, and intracranial hypertension.

Psychiatric:

Psychosis, hallucinations, disorientation, depression, and anxiety.

Respiratory:

Cough, shortness of breath, and pulmonary infiltrates. (See WARNINGS)

Vascular:

Angioedema, arteritis, and vasculitis.

Miscellaneous:

Edema, (including periorbital), pyrexia, drowsiness, weakness, fatigue, lassitude, rigors, flushing, hearing loss, insomnia, and pneumonitis.

Overdosage:

No information is available on a specific result of overdose with erythromycin ethylsuccinate and sulfisoxazole acetyl for oral suspension. Overdosage of erythromycin should be handled with the prompt elimination of unabsorbed drug and all other appropriate measures. Erythromycin is not removed by peritoneal dialysis or hemodialysis.

The amount of a single dose of sulfisoxazole that is either associated with symptoms of overdosage or is likely to be life-threatening has not been reported. Signs and symptoms of overdosage reported with sulfonamides include anorexia, colic, nausea, vomiting, dizziness, headache, drowsiness and unconsciousness. Pyrexia, hematuria and crystalluria may be noted. Blood dyscrasias and jaundice are potential late manifestations of overdosage.

General principles of treatment include the immediate discontinuation of the drug, instituting gastric lavage or emesis, forcing oral fluids, and administering intravenous fluids if urine output is low and renal function is normal. The patient should be monitored with blood counts and appropriate blood chemistries, including electrolytes. If the patient becomes cyanotic, the possibility of methemoglobinemia should be considered and, if present, the condition should be treated appropriately with intravenous 1% methylene blue. If a significant blood dyscrasia or jaundice occurs, specific therapy should be instituted for these complications. Peritoneal dialysis is not effective, and hemodialysis is only moderately effective in removing sulfonamides.

The acute toxicity of sulfisoxazole in animals is as follows:

Species | LD50=S.E.; (mg/kg)
mouse | 5700 = 235
rats | ± 10,000
rabbits | ± 2000

DOSAGE AND ADMINISTRATION:

ERYTHROMYCIN ETHYLSUCCINATE AND SULFISOXAZOLE ACETYL FOR ORAL SUSPENSION SHOULD NOT BE ADMINISTERED TO INFANTS UNDER 2 MONTHS OF AGE BECAUSE OF CONTRAINDICATIONS OF SYSTEMIC SULFONAMIDES IN THIS AGE GROUP.

For Acute Otitis Media in Children:

The dose of erythromycin ethylsuccinate and sulfisoxazole acetyl for oral suspension can be calculated based on the erythromycin component (50 mg/kg/day) or the sulfisoxazole component (150 mg/kg/day to a maximum of 6 g/day). The total daily dose of erythromycin ethylsuccinate and sulfisoxazole acetyl for oral suspension should be administered in equally divided doses three or four times a day for 10 days. Erythromycin ethylsuccinate and sulfisoxazole acetyl for oral suspension may be administered without regard to meals.

The following approximate dosage schedules are recommended for using erythromycin ethylsuccinate and sulfisoxazole acetyl for oral suspension:

Children:

Two months of age or older

FOUR-TIMES-A-DAY SCHEDULE
Weight | Dose - every 6 hours
Less than 8 kg (<18 lbs) | Adjust dosage by body weight
8 kg (18 lbs) | 1/2 teaspoonful (2.5 mL)
16 kg (35 lbs) | 1 teaspoonful (5 mL)
24 kg (53 lbs) | 1-1/2 teaspoonfuls (7.5 mL)
Over 32 kg (over 70 lbs) | 2 teaspoonfuls (10 mL)
THREE-TIMES-A-DAY SCHEDULE
Weight | Dose - every 8 hours
Less than 6 kg (>13 lbs) | Adjust dosage by body weight
6 kg (13 lbs) | 1/2 teaspoonful (2.5 mL)
12 kg (26 lbs) | 1 teaspoonful (5 mL)
18 kg (40 lbs) | 1-1/2 teaspoonfuls (7.5 mL)
24 kg (53 lbs) | 2 teaspoonfuls (10 mL)
Over 30 kg (over 66 lbs) | 2-1/2 teaspoonfuls (12.5 mL)

HOW SUPPLIED:

Erythromycin Ethylsuccinate and Sulfisoxazole Acetyl for Oral Suspension is available for teaspoon dosage in 100 mL (NDC 21695-690-00) bottles, in the form of granules to be reconstituted with water. The suspension provides erythromycin ethylsuccinate equivalent to 200 mg erythromycin activity and sulfisoxazole acetyl equivalent to 600 mg sulfisoxazole per teaspoonful (5 mL).

STORAGE AND HANDLING

Store at room temperature in dry form.

REFERENCES:

1. Biovert A, Barbeau G. Belanger PM: Pharmacokinetics of sulfisoxazole in young and elderly subjects. Gerontology 1984; 30: 125-131.
2. Oie S. Gambertoglio JG, Fleckenstein L: Comparison of the disposition of total and unbound sulfisoxazole after single and multiple dosing. J Pharmacokinet Biopharm 1982; 10: 157 - 172.
3. National Committee for Clinical Laboratory Standards: Performance Standards for Antimicrobial Disk Susceptibility Tests, ed 4. Approved Standard NCCLS Document M2-A4, Vol 10, No. 7. Villanova, Pa: NCCLS, 1990.

Manufactured by Duramed Pharmaceuticals, Inc.
Packaged by Pharmaceutics International, Inc.
Hunt Valley, Maryland 21031
for Duramed Pharmaceuticals, Inc.
Subsidiary of Barr Pharmaceuticals, Inc.
Pomona, NY 10970

Revised MARCH 2007
BR-0445

Repackaged by:

Rebel Distributors Corp

Thousand Oaks, CA 91320